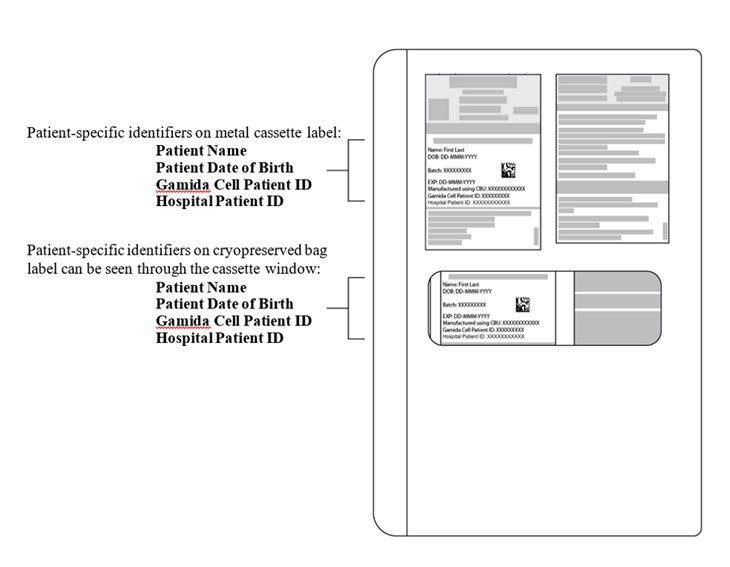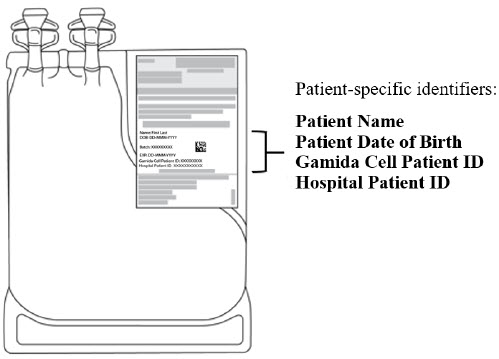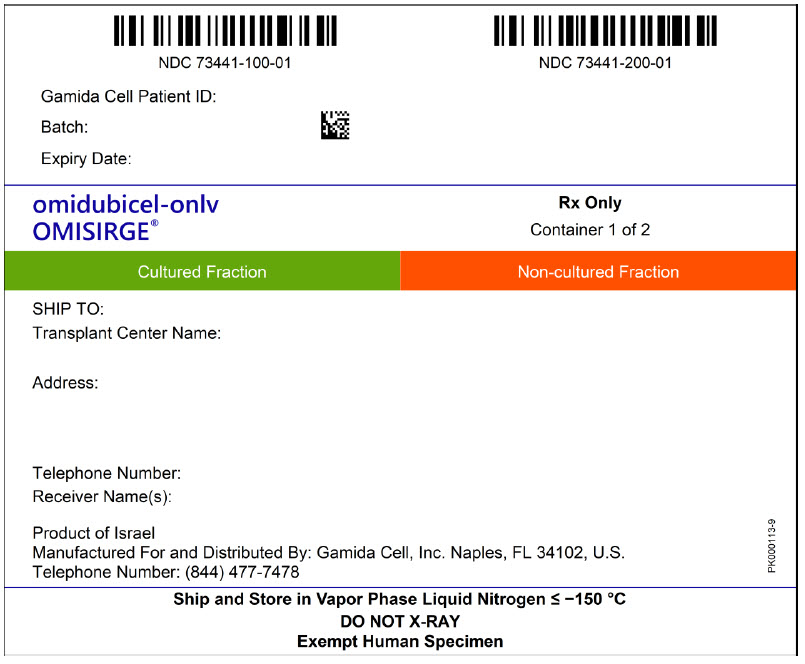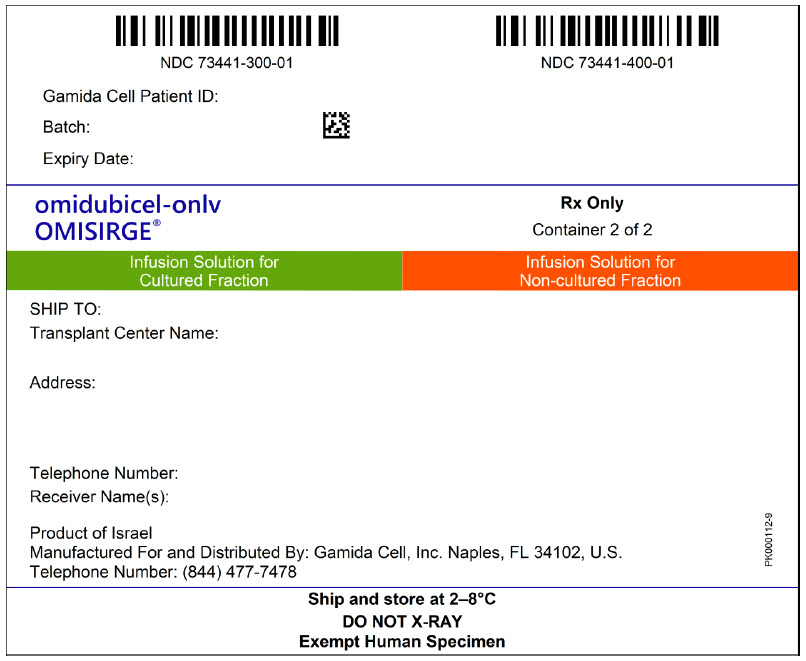 DRUG LABEL: OMISIRGE
NDC: 73441-800 | Form: KIT | Route: INTRAVENOUS
Manufacturer: Gamida Cell Inc.
Category: other | Type: CELLULAR THERAPY
Date: 20260219

ACTIVE INGREDIENTS: OMIDUBICEL 800000000 1/100 mL; OMIDUBICEL NON-CULTURED FRACTION 400000000 1/50 mL
INACTIVE INGREDIENTS: DIMETHYL SULFOXIDE; WATER; ALBUMIN HUMAN; DEXTRAN 40; DIMETHYL SULFOXIDE; WATER; ALBUMIN HUMAN; DEXTRAN 40

HIGHLIGHTS OF PRESCRIBING INFORMATION

These highlights do not include all the information needed to use OMISIRGE safely and effectively. See full prescribing information for OMISIRGE.
OMISIRGE® (omidubicel-onlv) Suspension for Intravenous Use
Initial U.S. Approval: 2023

WARNING: GRAFT VERSUS HOST DISEASE, INFUSION REACTIONS, AUTOIMMUNE CYTOPENIAS, GRAFT FAILURE, and ENGRAFTMENT SYNDROME

See full prescribing information for complete boxed warning.

- Graft-vs-Host Disease (GvHD): GvHD may be fatal. Administration of immunosuppressive therapy may decrease the risk of GvHD. (5.1)
- Infusion reactions: Infusion reactions may be fatal. Monitor patients during infusion and discontinue for severe reactions. Use is contraindicated in patients with known allergy to dimethyl sulfoxide (DMSO), Dextran 40, gentamicin, human serum albumin, or bovine material. (4, 5.2)
- Autoimmune cytopenias: Autoimmune cytopenias have occurred following treatment of severe aplastic anemia. Monitor blood counts prior to and after infusion. Manage cytopenias according to local institutional guidelines. (5.3)
- Graft failure: Graft failure may be fatal. Monitor patients for laboratory evidence of hematopoietic recovery. (5.4)
- Engraftment syndrome: Engraftment syndrome may be fatal. Treat engraftment syndrome promptly with corticosteroids. (5.6)

RECENT MAJOR CHANGES

Boxed Warning | 12/2025
Indication and Usage, Severe Aplastic Anemia (1.2) | 12/2025
Dosage and Administration (2.2) | 02/2026
Warning and Precautions (5.1, 5.2, 5.3, 5.4, 5.5) | 12/2025

1 INDICATIONS AND USAGE

OMISIRGE is a nicotinamide modified allogeneic hematopoietic progenitor cell therapy derived from cord blood indicated for the treatment of:

- adults and pediatric patients 12 years and older with hematologic malignancies who are planned for umbilical cord blood transplantation following myeloablative conditioning to reduce the time to neutrophil recovery and the incidence of infections. (1.1)
- adults and pediatric patients 6 years and older with severe aplastic anemia (SAA) following reduced intensity conditioning. (1.2)

2 DOSAGE AND ADMINISTRATION

For intravenous use only.

Do not irradiate.

- Do not use a leukodepleting filter. (2)
- Verify patient's identity upon receipt, prior to thaw and prior to infusion. (2)
- Thawing should only take place immediately prior to use. (2)
- Premedicate the patient approximately 30 to 60 minutes prior to infusion. (2)
- The recommended dose of OMISIRGE is a one-time infusion delivered in two separate bags. (2)
- The CF (Cultured Fraction) bag must be administered FIRST, and infusion should not exceed 2 hours from the end of dilution. Infusion of the NF (Non-cultured) bag should not exceed 1 hour from the end of dilution. (2)
- Administration of OMISIRGE should be under the supervision of a physician experienced in treatment of hematologic malignancies or SAA, as appropriate, in centers with expertise in hematopoietic stem cell transplants. (2)
- See full prescribing information for details for preparation and administration of OMISIRGE.

3 DOSAGE FORMS AND STRENGTHS

A single dose of OMISIRGE consists of

- a Cultured Fraction (CF): a minimum of 8.0 × 10^8 total viable cells of which a minimum of 8.7% is CD34+ cells and a minimum of 9.2 × 10^7 CD34+ cells, and
- a Non-cultured Fraction (NF): a minimum of 4.0 × 10^8 total viable cells with a minimum of 2.4 × 10^7 CD3+ cells. (3)

4 CONTRAINDICATIONS

Known sensitivity to dimethyl sulfoxide (DMSO), Dextran 40, gentamicin, human serum albumin or bovine material. (4)

5 WARNINGS AND PRECAUTIONS

- Malignancies of donor origin: Monitor life-long for secondary malignancies. In the event that a secondary malignancy occurs after treatment with OMISIRGE, contact Gamida Cell at (844) 477-7478. (5.5)
- Transmission of serious infections: Monitor patients closely for serious infections. (5.7)
- Transmission of rare genetic diseases: Monitor patients for rare genetic diseases. (5.8)

6 ADVERSE REACTIONS

- Hematological malignancies: The most common adverse reactions (incidence > 20%) are infections, GvHD, and infusion and hypersensitivity reactions. (6.1)
- SAA: The most common adverse reactions (incidence > 20%) are infections, hyperglycemia, skin rash, febrile neutropenia, immune thrombocytopenia, acute kidney injury, acute GvHD, hypertension, hypoxia, and infusion related reactions. (6.1)

To report SUSPECTED ADVERSE REACTIONS, contact Gamida Cell at (844) 477-7478 or FDA at 1-800-FDA-1088 or www.fda.gov/medwatch.

FULL PRESCRIBING INFORMATION

WARNING: GRAFT VERSUS HOST DISEASE, INFUSION REACTIONS, AUTOIMMUNE CYTOPENIAS, GRAFT FAILURE, and ENGRAFTMENT SYNDROME

- Graft-vs-Host Disease (GvHD): GvHD may be fatal. Administration of immunosuppressive therapy may decrease the risk of GvHD [see Warnings and Precautions (5.1)].
- Infusion reactions: Infusion reactions may be fatal. Monitor patients during infusion and discontinue for severe reactions. Use is contraindicated in patients with known allergy to dimethyl sulfoxide (DMSO), Dextran 40, gentamicin, human serum albumin, or bovine material [see Contraindications (4), Warnings and Precautions (5.2)].
- Autoimmune cytopenias: Autoimmune cytopenias have occurred following treatment of severe aplastic anemia. Monitor blood counts prior to and after infusion. Manage cytopenias according to local institutional guidelines [see Warnings and Precautions (5.3)].
- Graft failure: Graft failure may be fatal. Monitor patients for laboratory evidence of hematopoietic recovery [see Warnings and Precautions (5.4)].
- Engraftment syndrome: Engraftment syndrome may be fatal. Treat engraftment syndrome promptly with corticosteroids [see Warnings and Precautions (5.6)].

1 INDICATIONS AND USAGE

1.1 Hematologic Malignancies

OMISIRGE is indicated for the treatment of adults and pediatric patients 12 years and older with hematologic malignancies who are planned for umbilical cord blood transplantation following myeloablative conditioning to reduce the time to neutrophil recovery and the incidence of infections.

1.2 Severe Aplastic Anemia

OMISIRGE is indicated for the treatment of adults and pediatric patients 6 years of age and older with severe aplastic anemia (SAA) following reduced intensity conditioning.

2 DOSAGE AND ADMINISTRATION

2.1 Dose

For intravenous use only.

The recommended dose of OMISIRGE is a one-time infusion delivered in two separate bags which consists of

- a Cultured Fraction (CF): a minimum of 8.0 × 10^8 total viable cells of which a minimum of 8.7% is CD34+ cells and a minimum of 9.2 × 10^7 CD34+ cells, and
- a Non-cultured Fraction (NF): a minimum of 4.0 × 10^8 total viable cells with a minimum of 2.4 × 10^7 CD3+ cells

The CF and NF are supplied cryopreserved. OMISIRGE requires thaw and dilution with two infusion solution (IS) bags (one IS bag for the CF, and one IS bag for the NF) prior to administration. Infusion of the NF bag should begin within 1 hour after completion of the CF infusion. For timing of dosing of each fraction, refer to section 2.2 under "Planning prior to OMISIRGE preparation".

2.2 Preparation and Administration

Administration of OMISIRGE should be under the supervision of a physician experienced in treatment of hematologic malignancies or SAA, as appropriate, in centers with expertise in hematopoietic stem cell transplants.

Preparation

Pretreatment

- Confirm the Release For Infusion Certificate (RFI Certificate) is available for OMISIRGE before starting the conditioning regimen.
- Before infusion of OMISIRGE, administer as appropriate:
  - For patients with hematologic malignancies, administer a myeloablative conditioning regimen according to institutional guidelines.
  - For patients with SAA, administer a reduced intensity conditioning regimen according to institutional guidelines.
- Administer prophylactic and supportive therapies [including Granulocyte-Colony Stimulating Factor (G-CSF)] for prevention or treatment of transplant complications (GvHD, infections) according to institutional guidelines.
  Confirm emergency medications are available prior to infusion and during the recovery period as per institutional guidelines.

Premedication for Patients with Hematologic Malignancies

- Premedicate the patient approximately 30 to 60 minutes prior to OMISIRGE infusion.
- Premedicate with diphenhydramine 50 mg IV (or 0.5 mg/kg up to a maximum of 50 mg) or dexchlorpheniramine 10 mg IV, hydrocortisone 50 mg IV (or 0.5 mg/kg up to a maximum of 50 mg) and acetaminophen 650 mg PO (or 10 mg/kg up to a maximum of 650 mg).
- Avoid prophylactic use of methylprednisolone in conjunction with OMISIRGE.
- Ensure the patient is adequately hydrated.

Premedication for Patients with SAA

- For patients receiving Anti-thymocyte globulin (ATG) – administer oral prednisone at 1 mg/kg/day (or IV methylprednisolone if clinically indicated) 1 day prior to the first dose of ATG and continue according to institutional guidelines.
- Administer diphenhydramine 25-50 mg PO or IV and acetaminophen 650 mg PO or weight-based dosing for pediatric patients as per institutional guidelines, approximately 30 minutes prior to OMISIRGE infusion.
- Ensure the patient is adequately hydrated.

Receipt of OMISIRGE

Do not irradiate.

OMISIRGE is shipped directly to the transplant center in 2 shipping containers: [see How supplied/ Storage and Handling (16)]

1. A liquid nitrogen dry vapor shipper containing the CF, the NF and a Chimerism Testing Sample(s) at ≤ - 150℃.
2. A refrigerated shipping container containing the Infusion Solution for CF and the Infusion Solution for NF at 2-8℃.

- Confirm that the batch number and patient-specific identifiers on both shipping container labels match the intended patient and the information on the documents from the Gamida Cell Assist Hospital Portal.
- Confirm receipt of the Release for Shipping Certificate. Confirm patient-specific identifiers on the RFI Certificate and Certificates of Analysis (CoAs) match the patient's identity.
- Ensure that OMISIRGE was received in appropriate conditions and confirm that the temperature of the liquid nitrogen dry vapor shipper upon receipt was ≤ -150℃ and the temperature of the refrigerated shipping container was 2-8℃.
- If either of the shippers have expired upon arrival, or if you cannot confirm the patient identity with the patient-specific identifiers on any of the labels, contact Gamida Cell at (844) 477-7478.
- You should receive a total of 4 bags [i.e., CF Drug Product (DP) bag, NF DP bag, IS bag for CF DP and IS bag for NF DP] and vial or segment(s) containing Chimerism Testing Sample(s) in the OMISIRGE shipment.

The liquid nitrogen dry vapor shipper contains two metal cassettes, one labeled for the CF containing the CF cryopreserved bag and one labeled for the NF containing the NF cryopreserved bag. The shipper also contains a Chimerism Testing Sample(s).

- Verify that the products are within their expiry date by checking the label located on the front of the metal cassettes on the cryopreserved bags.
- Verify that the patient-specific identifiers on the labels on the outside of the CF and NF metal cassettes and on the CF and NF cryopreserved bags (see Figure 1) match the intended patient.
- Transfer the metal cassettes containing the CF and NF cryopreserved bags and the Chimerism Testing Sample(s) to onsite vapor phase of liquid nitrogen storage at ≤ -150℃.

Figure 1: CF or NF Cryopreserved Bag inside closed Metal Cassette.
Patient-specific identifiers are visible on the cryopreserved bag and can be seen through the cassette window.

The refrigerated shipping container contains 2 IS bags, the IS for CF and the IS for NF, each with tubing and an attached spike adaptor. Each IS bag is packed inside a sterile bag.

- Ensure that both bags are intact and verify that the Infusion Solutions are within their expiry date by checking the expiration date on the labels located on the IS bags.
- Verify that the patient-specific identifiers on the IS bag labels match the intended patient (see Figure 2).
- Transfer both IS bags to refrigerated storage at 2-8°C.
  Figure 2: Infusion Solution for CF Bag with Patient-Specific Label.
  The IS bag has tubing with an attached spike adaptor and is packed inside a sterile bag.

Planning prior to OMISIRGE preparation

- OMISIRGE must not be prepared until after receipt of the RFI Certificate for this patient-specific batch of OMISIRGE. CoAs for the CF, NF and IS batches are attached to the RFI Certificate. The RFI certificate will be issued via Gamida Cell Assist Hospital Portal up to 72 hours after completion of manufacturing.
- Confirm receipt of the RFI Certificate. Confirm patient-specific identifiers on the RFI Certificate and CoAs match the patient's identity.
- The CF bag must be administered FIRST.
- Confirm the infusion time in advance and adjust the start time of CF cryopreserved bag thaw so that it will be available for infusion when the patient is ready.
- Once the CF cryopreserved bag is removed from the metal cassette, thawing and dilution must be carried to completion and the cells administered within 2 hours post-dilution.
- Do not thaw the NF cryopreserved bag until you have determined that the CF has been safely administered.
- Once the NF cryopreserved bag is removed from the metal cassette, thawing and dilution must be carried to completion and the cells administered within 1 hour post-dilution.
- The infusion of the NF bag should begin within 1 hour after completion of the CF infusion.

Preparation of OMISIRGE for Infusion

- Follow universal precautions and local biosafety guidelines for handling and disposal of human cells to avoid potential transmission of infectious diseases.
- Use aseptic technique for all processing steps, including spiking of all transfusion infusion bag ports. No samples should be drawn from OMISIRGE.

The Cultured Fraction

Preparation of the Infusion Solution for CF

1. Remove the IS for CF bag from the 2-8°C storage location. Remove only the IS for CF bag at this time.
2. Confirm patient-specific identifiers on the label of the IS for CF match the intended patient.
3. Wipe the IS for CF sterile bag with 70% alcohol. Place it in the Biological Safety Cabinet (BSC) (if available), for at least 20 minutes with a maximum of 24 hours at room temperature.
4. Prior to dilution, remove the IS for CF bag from its sterile bag. Check that the pinch clamp is closed.

Thawing and diluting the CF

5. Remove the CF metal cassette from the liquid nitrogen storage.
6. Prior to preparing the bag for infusion verify that the patient-specific identifiers on the label on the outside of the cassette and on the CF cryopreserved bag match the intended patient (see Figure 1).
7. Once patient identity has been verified, remove the CF cryopreserved bag from the cassette. Leave the CF cryopreserved bag in the overwrap bag during thawing and dilution.
8. Visually inspect the CF cryopreserved bag for damage. If the bag is damaged, contact Gamida Cell at (844) 477-7478. The cryopreserved CF should be white in color.
9. Once the CF cryopreserved bag is removed from the metal cassette, the thaw and dilution must be carried to completion and the cells administered within 2 hours post-dilution.
10. Incubate the CF cryopreserved bag for 5 minutes at room temperature.
11. Place the CF cryopreserved bag in an approximately 37°C water bath until the product reaches a liquid consistency. This generally takes about 3-8 minutes.

Do not massage, knead or apply pressure on the product bag. Keep the bag fully submerged until thawed – do not remove before thawing completion.

12. Remove the thawed bag from the water bath as soon as the cells have completely thawed. Do not remove the overwrap bag.
13. Wipe the overwrap with 70% alcohol. Put the bag into the BSC (if available).
14. Open the overwrap as follows:
  - Wipe a pair of clean scissors with 70% alcohol.
  - Cut the sealed area at the top of the overwrap.
    Be careful not to damage the CF bag or the CF bag's ports/ tubing.
15. Insert the spike adapter attached to the IS for CF bag into one of the ports of the CF bag, while it remains in the overwrap bag.
16. Open the pinch clamp on the IS tubing and double the volume of the CF by adding IS for CF (approximately 20 mL) to the CF bag. Gently swirl the bag until mixed well.
17. Add the remaining IS for CF (approximately 60 mL) to the CF bag. Close the valve and swirl gently.
18. Remove the overwrap of the CF bag and check the integrity of the CF bag.
19. Check the appearance of the contents of the CF bag. The thawed and diluted CF should appear as a yellowish suspension, essentially free of visible white clumps and foreign particulates.
20. Inspect the contents of the thawed and diluted CF bag for any visible cell clumps. If visible cell clumps remain, gently invert and/or massage the bag with fingertips. Small clumps of cellular material should disperse with gentle manual mixing. Do not infuse the CF if clumps are not dispersed, the bag is damaged or leaking, or otherwise appears to be compromised. If this occurs, call Gamida Cell at (844) 477-7478.
21. Heat seal and detach the emptied Infusion Solution for CF bag.
22. Connect the Transfusion Infusion Set to the free port on the CF bag. Alternatively, the infusion set may be connected in accordance with internal procedures.
23. Place the CF bag containing the thawed and diluted CF in a new sterile bag.

Note: Do not wash, spin down, and/or resuspend CF in new media prior to infusion.

24. Transport the product to the patient at room temperature. Unless prepared at the patient's bedside, transport the product to the bedside in a closed box/bag to protect the product during transport.
  The CF bag should be completely infused within 2 hours post-dilution.
25. See the ‘Administration’ section on how to infuse the CF.

The Non-cultured Fraction

Preparation of the Infusion Solution for NF

1. Remove the IS for NF bag from the 2-8°C storage location.
2. Repeat steps 2-4 from the CF process, for the IS for NF.

Thawing and diluting the NF

3. Repeat steps 5-8 from the CF process, for the NF. The cryopreserved NF should be red in color.
4. Once the NF cryopreserved bag is removed from the metal cassette, the thaw and dilution must be carried to completion and the cells administered within 1 hour post-dilution.
5. Repeat steps 10-14 from the CF process, for the NF.
6. Insert the spike adapter attached to the IS for NF bag into one of the ports of the NF bag, while it remains in the overwrap bag.
7. Open the pinch clamp on the IS tubing and double the volume of the NF by adding Infusion Solution for NF (approximately 10 mL) to the NF bag. Gently swirl the bag until mixed well.
8. Add the remaining IS for NF (approximately 30 mL) to the NF bag. Close the valve and swirl gently.
9. Repeat steps 18-21 from the CF process, for the NF. The thawed and diluted NF should appear as a reddish suspension essentially free of visible clumps and foreign particulates.
10. Repeat steps 22-25 from the CF process, for the NF. The NF should be completely infused within 1 hour post-dilution.

Administration

Do NOT use a leukodepleting filter

- Central venous access is recommended for the infusion of OMISIRGE.
- Confirm that the patient's identity matches the patient-specific identifiers on the CF and NF bags.
- Administer OMISIRGE by gravity infusion.
- Prior to spiking both the CF and NF bags, prime the infusion set tubing with normal saline.
- Infuse the entire contents of the CF and NF bags.
- The rate of infusion should not exceed a maximum of 10 mL per kg per hour.

Administration:

1. The thawed and diluted CF bag must be infused FIRST. The infusion time should not exceed 2 hours from the end of dilution to the end of CF infusion. Should an infusion reaction occur, appropriately manage the reaction before thawing the NF.
2. The thawed and diluted NF should be infused within 1 hour of safely administering the CF infusion. The infusion time should not exceed 1 hour from the end of dilution to the end of infusion.
3. In the event of any deviation from the dosing schedule, contact Gamida Cell at (844) 477-7478.
4. After the entire contents of the CF and NF bags are each infused, wash the tubing with normal saline at the same infusion rate to ensure as many cells as possible are delivered to the patient.

Follow universal precautions and local biosafety guidelines for handling and disposal of human cells to avoid potential transmission of infectious diseases.

Monitoring

- Monitor the patient for hypersensitivity or other infusion-related reactions during the infusion and post-infusion, per institutional guidelines.
- Reduce the infusion rate if the fluid load is not tolerated. Pause the infusion in the event of a hypersensitivity reaction or if the patient develops a moderate to severe infusion reaction. Administer appropriate medical therapy as needed. [See Warnings and Precautions (5.2)]
- Conduct frequent clinical and laboratory assessments and vital signs and monitor for graft failure, GvHD, infections and other post-transplant complications according to institutional guidelines.

3 DOSAGE FORMS AND STRENGTHS

A single dose of OMISIRGE consists of:

- a Cultured Fraction: At the time of cryopreservation, the CF contains a minimum of 8.0 × 10^8 total viable cells with a minimum of 8.7% CD34+ cells and a minimum of 9.2 × 10^7 CD34+ cells suspended in approximately 10% dimethyl sulfoxide (DMSO).
- a Non-cultured Fraction: At the time of cryopreservation, the NF contains a minimum of 4.0 × 10^8 total viable cells with a minimum of 2.4 × 10^7 CD3+ cells suspended in approximately 10% DMSO.

Each fraction is supplied separately in its own cryopreserved bag [see How Supplied/Storage and Handling (16)]. Both bags diluted with their respective IS must be infused to achieve the dose of OMISIRGE.

See the respective CoA for the CF and NF for actual cell counts. The CoAs are attached to the RFI Certificate available via the Gamida Cell Assist Hospital Portal.

Table 1: Appearance of OMISIRGE
Product Bags | Appearance Immediately before Thawing | Appearance Post-Dilution
Cultured Fraction | White, frozen at the bottom of the cryopreserved bag | Yellowish suspension, essentially free of visible white clumps and foreign particulates
Non-cultured Fraction | Red, frozen at the bottom of the cryopreserved bag | Reddish suspension, essentially free of visible clumps and foreign particulates

4 CONTRAINDICATIONS

OMISIRGE is contraindicated in patients with known hypersensitivity to dimethyl sulfoxide (DMSO), Dextran 40, gentamicin, human serum albumin, or bovine products.

5 WARNINGS AND PRECAUTIONS

5.1 Graft-versus-Host Disease

Acute and chronic graft-versus-host disease (GvHD) have occurred following treatment with OMISIRGE [see Adverse Reactions (6.1)]. Acute GvHD manifests as maculopapular rash, gastrointestinal symptoms, and elevated bilirubin. Chronic GvHD manifests as skin rash, oral symptoms, ocular dryness, transaminase elevations, gastrointestinal symptoms, or serositis.

Patients treated with OMISIRGE should receive immunosuppressive drugs to decrease the risk of GvHD, and be monitored for signs and symptoms of GvHD, and treated if GvHD develops.

5.2 Hypersensitivity and Infusion-Related Reactions

Hypersensitivity and infusion-related reactions have occurred with OMISIRGE administration [see Adverse Reactions (6.1)].

Serious hypersensitivity reactions, including anaphylaxis, may be due to DMSO, residual gentamicin, Dextran 40, human serum albumin (HSA) and bovine material in OMISIRGE. OMISIRGE may contain residual antibiotics if the cord blood donor was exposed to antibiotics in utero. Patients with a history of allergic reactions to antibiotics should be monitored for allergic reactions following OMISIRGE administration.

Signs and symptoms of hypersensitivity reactions may include bronchospasm, wheezing, angioedema, pruritus, hives, fever, and hypotension during or after OMISIRGE infusion.

Infusion-related reactions may begin within minutes of the start of infusion of OMISIRGE, although symptoms may continue to intensify and not peak for several hours after the completion of the infusion.

Premedicate patients with antipyretics, histamine antagonists, and corticosteroids and monitor closely for signs and symptoms of hypersensitivity and infusion-related reactions. When a reaction occurs, pause the infusion and institute supportive care as needed.

5.3 Autoimmune Cytopenias

Autoimmune cytopenias (AICs) have occurred with OMISIRGE administration in patients with SAA. AIC is characterized by thrombocytopenia, anemia, and neutropenia, alone or in combination, occurring weeks to months post-transplant, often after initial hematopoietic recovery.

Risk factors for post-transplant AIC include younger age, ATG-containing conditioning, underlying SAA, and delayed T cell chimerism.

Monitor blood counts prior to and after OMISIRGE infusion. Manage cytopenias according to local institutional guidelines.

5.4 Graft Failure

Graft failure has occurred with OMISIRGE administration [see Adverse Reactions (6.1)]. Primary graft failure, which may be fatal, is defined as failure to achieve an absolute neutrophil count greater than 500 per microliter blood by Day 42 after transplantation. Immunologic rejection is the primary cause of graft failure. Patients should be monitored for laboratory evidence of hematopoietic recovery.

5.5 Malignancies of Donor Origin

Malignancy of donor origin including post-transplant lymphoproliferative disorder (PTLD) has occurred with OMISIRGE administration. PTLD manifests as a lymphoma-like disease favoring non-nodal sites. PTLD is usually fatal if not treated. The etiology is thought to be donor lymphoid cells transformed by Epstein-Barr virus (EBV). Serial monitoring of blood for EBV DNA may be warranted in patients with persistent cytopenias.

A donor-cell derived myelodysplastic syndrome (MDS) has occurred with OMISIRGE administration. The natural history is presumed to be the same as that for de novo MDS. Monitor life-long for secondary malignancies.

In the event that a secondary malignancy occurs, contact Gamida Cell at (844) 477-7478.

5.6 Engraftment Syndrome

Engraftment syndrome may occur because OMISIRGE is derived from umbilical cord blood. Monitor patients for unexplained fever, rash, hypoxemia, weight gain, and pulmonary infiltrates in the peri-engraftment period. Treat with corticosteroids as soon as engraftment syndrome is recognized to ameliorate symptoms. If untreated, engraftment syndrome may progress to multiorgan failure and death.

5.7 Transmission of Serious Infections

Transmission of infectious disease may occur because OMISIRGE is derived from umbilical cord blood. Disease may be caused by known or unknown infectious agents. Donors are screened for increased risk of infection with human immunodeficiency virus (HIV), human T-cell lymphotropic virus (HTLV), hepatitis B virus (HBV), hepatitis C virus (HCV), T. pallidum, West Nile virus (WNV), transmissible spongiform encephalopathy (TSE) agents, vaccinia, and Zika virus [for umbilical cord blood (UCB) collected between March 2016 and 20 May 2024]. Donors are also screened for clinical evidence of sepsis, and communicable disease risks associated with xenotransplantation. Maternal blood samples are tested for HIV types 1 and 2, HTLV types I and II, HBV, HCV, T. pallidum, and WNV. OMISIRGE is tested for sterility. There may be an effect on the reliability of the sterility test results if the cord blood donor was exposed to antibiotics in utero. OMISIRGE is tested for sterility, endotoxin, and mycoplasma. These measures do not totally eliminate the risk of transmitting these or other transmissible infectious diseases and disease agents.

Testing of maternal and infant donor blood is also performed for evidence of donor infection due to cytomegalovirus (CMV).

Test results may be found on the container label and/or in accompanying records.

Product manufacturing includes bovine-derived reagents. While all animal-derived reagents are tested for animal viruses, bacteria, fungi, and mycoplasma before use, these measures do not eliminate the risk of transmitting these or other transmissible infectious diseases and disease agents.

Final sterility test results may not be available at the time of use, but Quality Assurance (QA) will communicate any positive results from sterility testing to the physician. Report the occurrence of transmitted infection to Gamida Cell at (844) 477-7478.

5.8 Transmission of Rare Genetic Diseases

OMISIRGE may transmit rare genetic diseases involving the hematopoietic system because it is derived from umbilical cord blood. Cord blood donors have been screened to exclude donors with sickle cell anemia, and anemias due to abnormalities in hemoglobins C, D, and E. Because of the age of the donor at the time cord blood collection takes place, the ability to exclude rare genetic diseases is severely limited. Report the occurrence of transmitted rare genetic disease to Gamida Cell at (844) 477-7478.

6 ADVERSE REACTIONS

6.1 Clinical Trials Experience

Because clinical trials are conducted under widely varying conditions, adverse reaction rates observed in the clinical trials of a drug cannot be directly compared to rates in the clinical trials of another drug and may not reflect the rates observed in practice.

Hematologic Malignancies

The safety of OMISIRGE is based on data from Study P0501 for 52 patients transplanted with OMISIRGE and 56 patients transplanted with umbilical cord blood (UCB) [see Clinical Studies (14)]. The median duration of follow up for the overall safety population was 14 months (range, 1-19 months). All patients received myeloablative preparative regimens and GvHD prophylaxis with tacrolimus or cyclosporin plus mycophenolate mofetil.

Fatal adverse reactions occurred in 17% of patients treated with OMISIRGE, including infection (6%), acute GvHD (6%), veno-occlusive disease (VOD)/sinusoidal obstruction syndrome (SOS) (2%), thrombotic thrombocytopenic purpura (TTP)/thrombotic microangiopathy (TMA) (2%), and pulmonary hemorrhage (2%). Fatal adverse reactions occurred in 29% of subjects treated with UCB, including infection/sepsis (11%), respiratory disorders (11%), GvHD (5%), and VOD/SOS (2%).

The most common non-laboratory adverse reactions occurring in ≥ 10% of patients in Study P0501 are listed in Table 2 below. The most common Grade 3-5 adverse reactions for patients treated with OMISIRGE, were pain (33%), mucosal inflammation (31%), hypertension (25%), and gastrointestinal toxicity (19%).

Table 2: Adverse Reactions in ≥ 10% of Patients with Hematologic Malignancies Following Transplantation with OMISIRGE (N=52) or UCB (N=56) in Study P0501
Adverse Reaction | OMISIRGE Any Grade n (%) | OMISIRGE Grade 3 or Higher n (%) | UCB Any Grade n (%) | UCB Grade 3 or Higher n (%)
General disorders and administration site conditions | - | - | - | -
Pain | 41(79) | 17 (33) | 43 (77) | 10 (18)
Fever | 42 (81) | 1 (2) | 54 (96) | 6 (11)
Mucosal inflammation | 39 (75) | 16 (31) | 47 (84) | 19 (34)
Fatigue [Fatigue includes asthenia and fatigue.] | 31(60) | 2 (4) | 42 (75) | 12 (21)
Edema | 24 (46) | 1 (2) | 37 (66) | 4 (7)
Chills | 19 (37) | 0 | 32 (57) | 0
Gastrointestinal disorders | - | - | - | -
Gastrointestinal toxicity | 40 (77) | 10 (19) | 48 (86) | 19 (34)
Vomiting | 33 (63) | 3 (6) | 40 (71) | 2 (4)
Dysphagia | 17 (33) | 6 (12) | 21 (38) | 7 (13)
Constipation | 12 (23) | 0 | 21 (38) | 0
Dyspepsia | 12 (23) | 0 | 12 (21) | 0
Abdominal distention | 10 (19) | 0 | 16 (29) | 1 (2)
Infections and infestations [Infections and infestations were graded according to the BMT-CTN grading system.] | - | - | - | -
Viral infections | 39 (75) | 4 (8) | 45 (80) | 15 (27)
Bacterial infections | 34 (65) | 4 (8) | 45 (80) | 13 (23)
Fungal infections | 11 (21) | 3 (6) | 15 (27) | 10 (18)
Immune System Disorder | - | - | - | -
Acute Graft versus host disease [Acute Graft-versus-host disease was graded according to the Consensus Conference on Acute GvHD grading.] | 32 (62) | 8 (15) | 24 (43) | 12 (21)
Chronic Graft versus host disease [Chronic Graft-versus-host disease was graded according to the 2014 NIH consensus criteria.] | 18 (35) | 12 (23) | 14 (25) | 11 (20)
Vascular disorders | - | - | - | -
Hypertension | 29 (56) | 13 (25) | 37 (66) | 21 (38)
Hemorrhage [Hemorrhage include cystitis hemorrhagic, epistaxis, gastrointestinal hemorrhage, hemorrhage, pulmonary alveolar hemorrhage, subarachnoid hemorrhage, and upper gastrointestinal hemorrhage.] | 25 (48) | 6 (12) | 34 (61) | 10 (18)
Hypotension | 16 (31) | 2 (4) | 19 (34) | 5 (9)
Psychiatric disorders | - | - | - | -
Insomnia | 24 (46) | 1 (2) | 26 (46) | 2 (4)
Anxiety | 15 (29) | 1 (2) | 21(38) | 3 (5)
Depression | 13 (25) | 0 | 16 (29) | 2 (4)
Cardiac Disorders | - | - | - | -
Arrythmia | 24 (46) | 0 | 30 (54) | 1 (2)
Investigations | - | - | - | -
Weight decrease/Decreased appetite | 23 (44) | 4 (8) | 22 (39) | 1 (2)
Musculoskeletal and connective tissue disorders | - | - | - | -
Muscular weakness | 16 (31) | 1 (2) | 22 (39) | 2 (4)
Nervous system disorder | - | - | - | -
Dysgeusia | 15 (29) | 0 | 9 (16) | 0
Dizziness | 10 (19) | 0 | 13 (23) | 0
Tremor | 8 (15) | 0 | 12 (21) | 1 (2)
Somnolence | 7 (13) | 1 (2) | 12 (21) | 0
Respiratory, thoracic, and mediastinal disorders | - | - | - | -
Cough | 14 (27) | 0 | 30 (54) | 0
Dyspnea | 13 (25) | 4 (8) | 26 (46) | 9 (16)
Dehydration | 11 (21) | 3 (6) | 10 (18) | 2 (4)
Respiratory Failure [Respiratory failure includes acute respiratory distress syndrome, acute respiratory failure, hypoxia, and respiratory failure.] | 8 (15) | 6 (12) | 26 (46) | 17 (30)
Neoplasms benign, malignant and unspecified (incl cysts and polyps) | - | - | - | -
Disease recurrence | 11 (21) | 8 (15) | 7 (13) | 5 (14)
Renal and urinary disorders | - | - | - | -
Renal impairment [Renal impairment includes acute kidney injury, blood creatinine increased and renal failure.] | 9 (17) | 6 (12) | 3 (5) | 3 (5)
Eye disorders | - | - | - | -
Dry eyes | 6 (12) | 0 | 10 (18) | 0
Injury, poisoning and procedural complications | - | - | - | -
Primary graft failure | 1 (2) | 1 (2) | 6 (11) | 6 (11)
Secondary graft failure | 1 (2) | 1 (2) | 0 | 0
Abbreviation: n: number; UCB: umbilical cord blood.

Table 3 summarizes selected chemistry abnormalities by treatment arm for patients treated in Study P0501.

Table 3: Chemistry Laboratory Abnormalities in ≥10% of Patients in Study P0501
 | OMISIRGE N = 52 |  | UCB N = 56
Laboratory Abnormality | Grade 1-4 % | Grade 3-4 % | Grade 1-4 % | Grade 3-4 %
Decreased magnesium | 94 | 4 | 91 | 2
Increased aspartate aminotransferase | 56 | 13 | 61 | 7
Increased alanine aminotransferase | 56 | 13 | 57 | 9
Increased creatinine | 50 | 4 | 57 | 2
Increased bilirubin | 42 | 12 | 61 | 21
Increased alkaline phosphatase | 42 | 0 | 54 | 2
Increased magnesium | 15 | 2 | 29 | 9
Abbreviation: N: number; UCB: umbilical cord blood.

Severe Aplastic Anemia

The safety data described in this section reflects exposure of OMISIRGE in one clinical study (Study 17-H-0091) for the treatment of severe aplastic anemia (SAA). A total of 17 patients received a single dose of OMISIRGE with a median dose of 8.5 × 10^6 cells/kg CD34+ cells (range, 2.3- 21.4 cells/kg CD34+ cells). Three out of 17 patients received OMISIRGE with haploidentical CD34+ cells [see Clinical Studies (14)]. All patients received a reduced intensity preparative conditioning regimen of cyclophosphamide, fludarabine, TBI and horse-ATG, and GvHD prophylaxis according to institutional guidelines. The median duration of follow-up was 25 months (range, 2-60 months).

Serious adverse reactions were reported in 15 patients including infections (n=15), diarrhea (n=3), nausea/vomiting (n=4), pyrexia (n=2), hypoxia (n=2), thrombotic microangiopathy (n=1), cardiac arrest (n=1), pericarditis (n=1), colitis (n=1), febrile neutropenia (n=1), cholecystitis (n=1), portal vein thrombosis (n=1), graft-versus-host disease (n=1), weight decreased (n=1), dehydration (n=1), Guillain-Barre Syndrome (n=1), uterine hemorrhage (n=1), pleural effusion (n=1), pulmonary hemorrhage (n=1), and respiratory failure (n=1).

One patient (6%) treated with OMISIRGE had a fatal adverse event. The patient engrafted but died on Day 62 from disseminated adenovirus infection.

Common Terminology Criteria for Adverse Events (CTCAE) Grade 3-5 non-laboratory adverse reactions in the SAA Study with greater or equal to 15% incidence are summarized in Table 4. The most common Grade 3-5 adverse reactions for patients treated with OMISIRGE were febrile neutropenia (41%), bacterial infections (41%), hyperglycemia (41%), Epstein-Barr virus infection (29%), immune thrombocytopenia (24%) and pneumonia (24%).

Table 4: Adverse Reactions in ≥15% of Patients with SAA Following Transplantation with OMISIRGE (N=17) in Study 17-H-0091
Adverse Reaction | OMISIRGE Any Grade n (%) | OMISIRGE Grade 3 or Higher n (%)
Infections and infestations | - | -
Human herpesvirus 6 infection | 16 (94) | 0
BK virus infection | 13 (76) | 0
Bacterial infections [Includes skin infection, Clostridium difficile infection, device related infections and urinary tract infections.] | 10 (59) | 7 (41)
Epstein-Barr virus infection | 9 (53) | 5 (29)
Cytomegalovirus infection [Is a composite that includes multiple related terms.] | 8 (47) | 3 (18)
Pneumonia | 6 (35) | 4 (24)
Adenovirus infection | 4 (24) | 1 (6)
Rhinovirus infection | 4 (24) | 1 (6)
Sepsis | 3 (18) | 3 (18)
Upper respiratory tract infection | 3 (18) | 1 (6)
Metabolism and nutrition disorders | - | -
Hyperglycemia | 11 (65) | 7 (41)
Hypertriglyceridemia | 3 (18) | 2 (12)
Skin and subcutaneous tissue disorders | - | -
Skin rash | 8 (47) | 0
Blood and lymphatic system disorders | - | -
Febrile neutropenia | 7 (41) | 7 (41)
Immune thrombocytopenia | 4 (24) | 4 (24)
Injury, poisoning and procedural complications | - | -
Infusion related reaction [Includes hypertension, headache and hypoxia.] | 4 (24) | 2 (12)
Immune system disorders | - | -
Acute graft-versus-host disease | 4 (24) | 1 (6)
Respiratory, thoracic and mediastinal disorders | - | -
Hypoxia | 4 (24) | 3 (18)
Respiratory failure [Includes dyspnea, respiratory distress and respiratory failure.] | 3 (18) | 3 (18)
Vascular disorders | - | -
Hypertension | 4 (24) | 3 (18)
Renal and urinary disorders | - | -
Acute kidney injury | 4 (24) | 2 (12)
Gastrointestinal disorders | - | -
Diarrhea | 3 (18) | 3 (18)
Nausea | 3 (18) | 2 (12)
Vomiting | 3 (18) | 2 (12)
Abbreviation: n: number.

Other clinically significant adverse reactions occurring in <15% of patients include the following: Post-transplant lymphoproliferative disorder in two patients (12%), primary graft failure (defined as failure to achieve an absolute neutrophil count ≥500 cells / µl for 3 consecutive measurements on different days) in 1 patient (6%), and engraftment syndrome in 1 patient (6%).

Table 5 summarizes laboratory abnormalities that worsened from baseline in ≥ 15% of patients in Study 17-H-0091.

Table 5: Laboratory Abnormalities that Worsened from Baseline in ≥15% of Patients in Study 17-H-0091 (N=17)
Laboratory Abnormality | Grade 1-4 N (%) | Grade 3-4 N (%)
Decreased potassium | 5 (29) | 0
Increased potassium | 4 (24) | 1 (6)
Decreased phosphorous | 4 (24) | 0
Increased alanine aminotransferase | 3 (18) | 2 (12)
Abbreviation: N: number.

8 USE IN SPECIFIC POPULATIONS

8.1 Pregnancy

Risk Summary

There are no available data with OMISIRGE use in pregnant women. No animal reproductive and developmental toxicity studies have been conducted with OMISIRGE to assess whether it can cause fetal harm when administered to a pregnant woman. In Study 17-H-0091, one patient reported two pregnancies, one at 9 months and one at 3.5 years post-transplant. There were no reported birth complications or neonatal concerns.

OMISIRGE should be used during pregnancy only if the potential benefit justifies the potential risk to the fetus.

In the United States (U.S.) general population, the estimated background risk of major birth defects and miscarriage in clinically recognized pregnancies is 2-4% and 15-20%, respectively.

8.2 Lactation

Risk Summary

There is no information regarding the presence of OMISIRGE in human milk, the effect on the breastfed infant, and the effects on milk production. The developmental and health benefits of breastfeeding should be considered along with the mother's clinical need for OMISIRGE and any potential adverse effects on the breastfed infant from OMISIRGE or from the underlying maternal condition.

8.3 Females and Males of Reproductive Potential

Pregnancy Testing

Pregnancy status of females with reproductive potential should be verified. Sexually active females of reproductive potential should have a pregnancy test prior to starting the conditioning regimen for OMISIRGE.

Contraception

See the prescribing information for the medications used for conditioning for information on the need for effective contraception in patients who receive a conditioning regimen.

There are insufficient exposure data to provide a recommendation concerning duration of contraception following treatment with OMISIRGE.

Infertility

There are no data on the effect of OMISIRGE on fertility.

8.4 Pediatric Use

The safety and efficacy of OMISIRGE have been established in pediatric patients with hematologic malignancy 12 years of age and older and in pediatric patients with severe aplastic anemia (SAA) 6 years of age and older.

The use of OMISIRGE in pediatric patients with hematologic malignancy was supported by evidence from one clinical study (Study P0501) which included 2 pediatric patients age 12 to 16 years. The use of OMISIRGE in pediatric patients with SAA was supported by evidence from one clinical study (Study 17-H-0091) which included 7 pediatric patients 6 to 16 years of age.

8.5 Geriatric Use

Clinical studies of OMISIRGE did not include patients aged 65 and over; therefore, it cannot be determined whether patients 65 years and over respond differently from younger patients.

11 DESCRIPTION

OMISIRGE (omidubicel-onlv) is a cryopreserved nicotinamide modified unrelated allogeneic hematopoietic progenitor cell therapy derived from cord blood consisting of 2 cell fractions; a Cultured Fraction (CF) and a Non-cultured Fraction (NF) which are both derived from the same patient-specific cord blood unit (CBU).

1) The CF is a yellowish suspension consisting of allogeneic, hematopoietic CD34+ progenitor cells.

In addition to the CD34+ hematopoietic progenitor cells (HPCs), the CF consists of other cell populations, including more differentiated myelomonocytic cells, dendritic cells and granulocytes. The CF formulation contains a maximum of 35 mg gentamicin. Following manipulation, the cells are washed, formulated into a suspension, and cryopreserved in a patient specific bag in 10% dimethyl sulfoxide (DMSO). The product is thawed and diluted prior to infusion [see Dosage and Administration (2.2), How Supplied/Storage and Handling (16)]. The CF contains approximately 2.42 mg of DMSO. The diluted CF contains ≤ 2% DMSO.

2) The NF is a reddish suspension consisting of allogeneic, hematopoietic mature myeloid and lymphoid cells that are washed, formulated into a suspension, and cryopreserved in a patient specific bag in 10% DMSO. In addition to the mature myeloid and lymphoid cells, the NF consists of other cell populations, including more lineage committed hematopoietic cells. The product is thawed and diluted prior to infusion [see Dosage and Administration (2.2), How Supplied/Storage and Handling (16)]. The NF contains approximately 1.1 mg of DMSO. The diluted NF contains ≤2% DMSO.

Two Infusion Solution bags are also provided for diluting each fraction after thawing, one specifically for the CF and one specifically for the NF. The Infusion Solutions contain 8% w/v HSA and 6.8% w/v Dextran 40 in 0.9% sodium chloride [see Dosage and Administration (2.2)].

The NF and IS are Released for Shipment (RFS) following full release testing, including sterility test. The CF is RFS at the end of manufacturing, prior to final product testing completion. OMISIRGE is Released for Infusion (RFI) after acceptable results from the CF's Rapid Contamination Test for microbial contamination and quantitative PCR-based mycoplasma test are obtained. The RFI includes all CF DP release testing as detailed in the CF CoA, except the pending Colony Forming Unit (CFU) and final Sterility tests results. RFI certificate is accompanied with the respective IS, NF, and CF CoA's. Receipt of the RFI Certificate for the patient-specific batch of OMISIRGE must be confirmed prior to preparation. RFI Certificate receipt is via the Gamida Cell Assist Hospital Portal, approximately 72 h of the end of manufacturing.

12 CLINICAL PHARMACOLOGY

12.1 Mechanism of Action

OMISIRGE is a nicotinamide (NAM) modified allogeneic hematopoietic progenitor cell therapy derived from cord blood used as an allogeneic stem cell donor source. OMISIRGE is manufactured utilizing a proprietary NAM based technology producing enriched HPCs.

NAM technology overcomes the induction of accelerated proliferation, differentiation, cellular stress and signaling pathways that are typically activated when HPCs are removed from their natural environment.

Ex-vivo culturing of cord blood derived HPCs in the presence of NAM leads to preservation of their stemness, homing to the bone marrow (BM) and retained engraftment capacity as demonstrated by rapid neutrophil engraftment and multi lineage immune reconstitution as observed in the clinical trials with OMISIRGE.

12.2. Pharmacodynamics

Transplantation with OMISIRGE resulted in rapid and broad immune reconstitution of dendritic cells, monocytes, Natural Killer (NK), CD4+ T cells and CD8+ T cells as early as one-week post-transplantation, and B cells 28 days post transplantation and all lineages throughout the one-year follow-up period. Robust positive linear correlations between the CD34(+) cell content in the OMISIRGE CF, and the reconstitution of T-cells and NK cells were identified. Additionally, dose-response analyses demonstrated a strong correlation between the total CD34+ cell counts and dose / kg for OMISIRGE with the kinetics of neutrophil recovery. The model demonstrated that days to neutrophil recovery decreased with an increase in OMISIRGE CD34(+) cell dose.

12.3 Pharmacokinetics

OMISIRGE is a cryopreserved nicotinamide modified allogeneic hematopoietic progenitor cell therapy derived from cord blood. The nature of OMISIRGE is such that conventional pharmacokinetic studies on absorption, distribution, metabolism, and excretion are not applicable.

13 NONCLINICAL TOXICOLOGY

13.1 Carcinogenesis, Mutagenesis, Impairment of Fertility

No in vivo carcinogenicity, mutagenicity and fertility studies were conducted to evaluate the effects of OMISIRGE.

14 CLINICAL STUDIES

14.1 Hematologic Malignancies

OMISIRGE was evaluated in Study P0501 (NCT02730299), an open-label, multicenter, randomized study of OMISIRGE transplantation or UCB transplantation following myeloablative conditioning in patients with hematologic malignancies.

In total, 125 patients with the availability of at least one ≥ 4/6 human leukocyte antigen (HLA)-matched (HLA-A, B and DR loci) cord blood unit were randomized to the study, 62 patients were randomized to receive OMISIRGE and 63 patients were randomized to the UCB group. The minimum specifications of OMISIRGE were a Total Nucleated Viable Cell (TNVC) count of 8.0 × 10^8 cells and CD34+ cell count of 5.6 × 10^7. Fifty-two patients were transplanted with OMISIRGE at a median CD34+ cell dose of 9.0 × 10^6 cells/kg (range 2.1 – 47.6 × 10^6 cells/kg). Fifty-six patients were transplanted in the UCB arm with one or two cord units (66% received two cord units); among patients in whom the post-thaw cell dose was reported (n = 42), the median CD34+ cell dose was 0.2 × 10^6 cells/kg (range 0.0 – 0.8 × 10^6 cells/kg). Multiple conditioning regimens were used, including Total Body Irradiation (TBI)-based or chemotherapy-based options.

Demographic and baseline patient characteristics were similarly distributed among the treatment arms. The overall study population included 72 males (58%) and 53 females (42%) with median age 41 years (range: 13–65). Fifty-eight percent of patients were White, 16% were Black, 14% were Asian and 13% were of other races or unknown. Thirteen percent of patients identified as Hispanic or Latino. Forty-eight percent of patients had Acute Myelogenous Leukemia (AML), 33% had Acute Lymphoblastic Leukemia (ALL), 7% had Myelodysplastic Syndrome (MDS), 5% had Chronic myeloid leukemia (CML), 4% had lymphoma and 3% had other rare leukemias. Baseline disease status (remission vs. overt disease) varied depending on the hematologic malignancy. Disease risk index was high/very high for 34% and moderate for 42%. HCT specific comorbidity index was ≥ 3 in 51% and 1-2 in 28% of patients.

Of the patients randomized to OMISIRGE, 8% of patients (5/62) were not able to receive OMISIRGE due to manufacturing failure.

The efficacy of OMISIRGE was established based on time to neutrophil recovery following transplantation and the incidence of BMT CTN Grade 2/3 bacterial or Grade 3 fungal infections through Day 100 following transplantation. The efficacy outcomes are summarized below.

Table 6: Efficacy Results in Patients Randomized to Receive OMISIRGE or UCB in Study P0501 (ITT Population)
Efficacy Outcome | OMISIRGE N=62 | UCB N=63 | Absolute Difference (95% CI)
Median time to neutrophil recovery [Time to neutrophil recovery was defined as the time from transplantation to the earliest of 3 consecutive measurements on different days with absolute neutrophil count greater than or equal to 0.5 Gi/L assessed with 42 days of follow-up.] , [Median time to neutrophil recovery was estimated by the Kaplan-Meier estimator.] | 12 days (95% CI: 10-15 days) | 22 days (95% CI: 19-25 days) | 10 days (95% CI: 6-14 days)
Incidence of Grade 2/3 bacterial or Grade 3 fungal infections through 100 days following transplantation | 39% | 60% | 22% (95% CI: 4%-39%)
Abbreviation: CI: Confidence interval; N: number; UCB: umbilical cord blood.

Eighty-seven percent of patients in the OMISIRGE arm and 83% in the UCB arm achieved neutrophil recovery. The median time to neutrophil recovery was 12 days in the OMISIRGE arm and 22 days in the UCB arm. BMT CTN Grade 2/3 bacterial or Grade 3 fungal infections through Day 100 following transplantation occurred in 39% of patients in the OMISIRGE arm and 60% of patients in the UCB arm.

Per Protocol Population:

Among the patients treated with OMISIRGE (n=52), neutrophil recovery with 42 days of follow-up was achieved in 94% of patients at a median of 10 days (95% CI: 8, 12), compared to 89% of patients treated with UCB (n=56), at a median of 20 days (95% CI: 18, 24). BMT CTN Grade 2/3 bacterial or Grade 3 fungal infections by 100 days were reported in 35% of patients treated with OMISIRGE and 61% of patients treated with UCB, respectively.

14.2 Severe Aplastic Anemia

The efficacy of OMISIRGE in patients with severe aplastic anemia (SAA) was evaluated in study 17- H-0091 (NCT 03173937), an open-label, single center study. The study enrolled patients with SAA who had intolerance or failure to respond to immunosuppressive therapy and availability of at least one ≥ 4/8 human leukocyte antigen (HLA)-matched (HLA-A, B, C and DR loci) cord blood unit. Patients were excluded if there was availability of an HLA identical (12/12) matched related or unrelated donor.

In total, 17 patients were treated with OMISIRGE, among them 14 patients were treated with OMISIRGE alone and three patients were treated with both OMISIRGE and haploidentical CD34+ cells. The minimum specifications of OMISIRGE were a Total Nucleated Viable Cell (TNVC) count of 8.0 × 10^8 cells and CD34+ cell count of 9.2 × 10^7. The fourteen patients who were transplanted with OMISIRGE alone were included in the efficacy evaluation. The median CD34+ cell dose of OMISIRGE was 9.5 × 10^6 cells/kg (range, 2.3 - 21.4 cells/kg). All patients received reduced intensity conditioning which included cyclophosphamide, fludarabine, TBI and horse-ATG. GvHD prophylaxis was administered according to institutional guidelines.

The demographic characteristic of the population included the following: median age was 17 years (range: 6 – 45), 10 patients (59%) were male, 6 patients (35%) were Black, 3 patients (18%) were White, 5 patients (29%) were Asian and 3 patients (18%) were of "other races" or "unknown". Twenty-nine percent of patients identified as Hispanic or Latino. Median absolute neutrophil count at baseline was 0.3 × 10^9/L (range, 0.0 – 1.0) and median platelet count at baseline was 35 × 10^9/L (range, 10-89). Hematopoietic stem cell transplantation (HSCT) specific comorbidity index was ≥ 3 in 76% and 0-2 in 24% of patients. Twelve percent of patients received 4/8 HLA match, 59% 5/8 HLA match, 18% 6/8 HLA match, 6% 7/8 HLA match and 6% 8/8 HLA match.

The primary efficacy outcome measure was the incidence of early and sustained neutrophil recovery, defined as ANC ≥500 cells/µl for 3 consecutive measurements on different days by Day 26, maintained at Days 42 and 100 posttransplant. Other secondary efficacy outcomes were neutrophil recovery (days to first of three consecutive ANC≥500 cells/µL), red blood cell (RBC) transfusion independence (days to 30-day transfusion independence), platelet recovery ≥20,000/µL (days to first of 3 consecutive platelet count of 20,000/µL with no preceding transfusion in 7 days) and platelet transfusion independence (days to 30-day platelet transfusion independence).

The efficacy results are summarized in Table 7 below.

Table 7: Efficacy Results from Study 17-H-0091
Efficacy Outcome | N=14
Patients with early and sustained neutrophil recovery at 100 days n (%) (95% CI) [95% CI was calculated by the Clopper-Pearson method.] | 12 (86%) (57%, 98%)
Time to neutrophil recovery [Time to neutrophil recovery was defined as ANC ≥500 cells/µl for 3 consecutive measurements on different days.] Median days (min - max) [Based on patients who achieved the events.] | 11 (7 – 20)
Time to RBC transfusion independence No. patients who achieved (%) Median days (min - max) | 12 (86%) 58.5 (42 – 446)
Time to platelet 20,000/µl recovery No. patients who achieved within a year (%) Median days (min – max) | 12 (86%) 31.5 (20 – 197)
Time to platelet transfusion independence No. patients who achieved (%) Median days (min - max) | 11 (79%) 53.0 (43 – 93)
Abbreviation: CI: Confidence interval; min: Minimum; max: Maximum; N: number.

16 HOW SUPPLIED/STORAGE AND HANDLING

OMISIRGE (NDC 73441-800-04) is shipped in two shipping containers, a liquid nitrogen dry vapor shipper at ≤ -150℃, containing the two cryopreserved cell fractions (CF NDC 73441-100-01 and NF NDC 73441-200-01) and a Chimerism Testing Sample(s) and a refrigerated shipping container at 2-8℃, containing two Infusion Solutions (Infusion Solution for CF NDC 73441-300-01 and Infusion Solution for NF NDC 73441-400-01). OMISIRGE is shipped to the transplant center for a specific patient.

The Cryopreserved Cell Fractions

OMISIRGE is comprised of two cryopreserved cell fractions, a Cultured Fraction (CF) and a Non-cultured Fraction (NF) each in a separate cryopreserved bag labeled for the specific patient. Each cryopreserved bag is protected by a corresponding transparent overwrap bag and each cryopreserved bag enclosed in its overwrap bag is individually packed in a metal cassette. Both cryopreserved OMISIRGE cell fractions are shipped together in the vapor phase of liquid nitrogen in a liquid nitrogen dry vapor shipper with the Prescribing Information (PI) and a Chimerism Testing Sample(s).

At the time of cryopreservation, the CF contains a minimum of 8.0 × 10^8 total viable cells with a minimum of 8.7% CD34+ cells and a minimum of 9.2 × 10^7 CD34+ cells suspended in 20 mL of a cryopreservation solution containing 10% DMSO.

See the CoA for the CF for actual cell counts. CoAs are attached to the RFI Certificate available via the Gamida Cell Assist Hospital Portal.

Upon cryopreservation, the CF appears white and is frozen at the bottom of the cryopreserved bag.

At the time of cryopreservation, the NF contains a minimum of 4.0 × 10^8 total viable cells with a minimum of 2.4 × 10^7 CD3+ cells suspended in 10 mL cryopreservation solution containing 10% DMSO.

See the CoA for the NF for actual cell counts.

Upon cryopreservation, the NF appears red and is frozen at the bottom of the cryopreserved bag.

- Match the identity of the patient with the patient-specific identifiers on the cassettes and cryopreserved bag labels upon receipt.
- Store OMISIRGE frozen in the vapor phase of liquid nitrogen (≤ -150°C) in a temperature-controlled system.
- Thaw immediately prior to use [see Dosage and Administration (2.2)].
- Use closed containers when transporting the bags within the facility.

STORAGE AND HANDLING

The Refrigerated Infusion Solutions

The Infusion Solutions (IS) used to dilute OMISIRGE CF and NF are provided in two IS bags labeled for the specific patient and for diluting the specific fraction. The IS for diluting the CF contains approximately 80 mL and the IS for diluting the NF contains approximately 40 mL of IS consisting of 6.8% Dextran 40 and 8% HSA. The Infusion Solutions are shipped in a refrigerated shipping container with the PI.

- Match the identity of the patient with the patient-specific identifiers on the IS bag labels upon receipt.
- Store the IS bags in a 2-8℃ refrigerated storage until the time of thaw of the OMISIRGE CF and NF.

17 PATIENT COUNSELING INFORMATION

Discuss the following with the patient receiving OMISIRGE:

The recommended course of therapy for OMISIRGE is a single dose for infusion, which is provided by the manufacturer as 2 separate components (CF and NF). OMISIRGE CF and OMISIRGE NF are infused one after the other once the patient has received an appropriate conditioning regimen.

Each OMISIRGE unit is specific to each patient. Ensure that patients understand the risk of manufacturing failure (8% in Study P0501) of OMISIRGE. In case of a manufacturing failure, a second manufacturing attempt may be considered. In this case, while the patient awaits the product, additional therapy (in addition to the preparative conditioning) may be necessary and may increase the risk of adverse events during the pre-infusion period.

Prior to infusion, advise patients of the following risks:

Graft-versus-Host Disease:

Report immediately any signs and symptoms suggestive of graft vs host disease, including rash, diarrhea or yellowing of the eyes [see Warnings and Precautions (5.1), Adverse Reactions (6.1)].

Hypersensitivity and Infusion-Related Reactions:

Report immediately any signs and symptoms of hypersensitivity reactions including wheezing, swelling, itching, or hives [See Warnings and Precautions (5.2)].

Report immediately any signs and symptoms of infusion reactions including fever, chills, fatigue, tachycardia, hypoxia, severe nausea, severe vomiting, diarrhea, muscle pain, joint pain, low blood pressure, high blood pressure, or dizziness/lightheadedness [see Warnings and Precautions (5.2), Adverse Reactions (6.1)].

Autoimmune Cytopenias

Report immediately any signs and symptoms of Autoimmune Cytopenias including pallor and fatigue, tachycardia (from anemia) and mild to moderate splenomegaly, petechiae, easy bruising or prolonged bleeding from cuts, and recurrent bacterial infections, persistent oral ulcers and gingivitis and frequent fevers [See Warnings and Precautions (5.3)].

Graft Failure:

Advise patients that primary graft failure, which may be fatal, can occur [See Warnings and Precautions (5.4), Adverse Reactions (6.1)].

Malignancies of Donor Origin:

Advise patients of the need to contact Gamida Cell at (844)-477-7478 if they are diagnosed with a secondary malignancy after treatment with OMISIRGE [See Warnings and Precautions (5.5), Adverse Reactions (6.1)].

Engraftment Syndrome:

Report immediately any signs and symptoms suggestive of engraftment syndrome including fever, rash, or unexplained weight gain [See Warnings and Precautions (5.6)].

Transmission of Serious Infections:

Advise patients of the risk of transmission of infectious disease [See Warnings and Precautions (5.7)].

Transmission of Rare Genetic Diseases:

Advise patients of the risk of transmission of rare genetic diseases [See Warnings and Precautions (5.8)].

Manufactured by:
Gamida Cell Ltd., Kiryat Gat 8258412, Israel
U.S. License number 2223

Distributed by:
Gamida Cell Inc., Naples, FL 34102

OMISIRGE® is a registered trademark of Gamida Cell Inc.
© Gamida Cell, Inc. All Rights Reserved.

PRINCIPAL DISPLAY PANEL - 20 mL and 10 mL Shipping Label

NDC 73441-100-01
NDC 73441-200-01

Gamida Cell Patient ID:
Batch:
Expiry Date:

omidubicel-onlv
OMISIRGE®

Rx Only
Container 1 of 2

Cultured Fraction
Non-cultured Fraction

SHIP TO:
Transplant Center Name:
Address:
Telephone Number:
Receiver Name(s):

Product of Israel
Manufactured For and Distributed By: Gamida Cell, Inc. Naples, FL 34102, U.S.
Telephone Number: (844) 477-7478

Ship and Store in Vapor Phase Liquid Nitrogen ≤ -150 °C
DO NOT X-RAY
Exempt Human Specimen

PK000113-9

PRINCIPAL DISPLAY PANEL - 80 mL and 40 mL Shipping Label

NDC 73441-300-01
NDC 73441-400-01

Gamida Cell Patient ID:
Batch:
Expiry Date:

omidubicel-onlv
OMISIRGE®

Rx Only
Container 2 of 2

Infusion Solution for
Cultured Fraction
Infusion Solution for
Non-cultured Fraction

SHIP TO:
Transplant Center Name:
Address:
Telephone Number:
Receiver Name(s):

Product of Israel
Manufactured For and Distributed By: Gamida Cell, Inc. Naples, FL 34102, U.S.
Telephone Number: (844) 477-7478

Ship and store at 2–8°C
DO NOT X-RAY
Exempt Human Specimen

PK000112-9